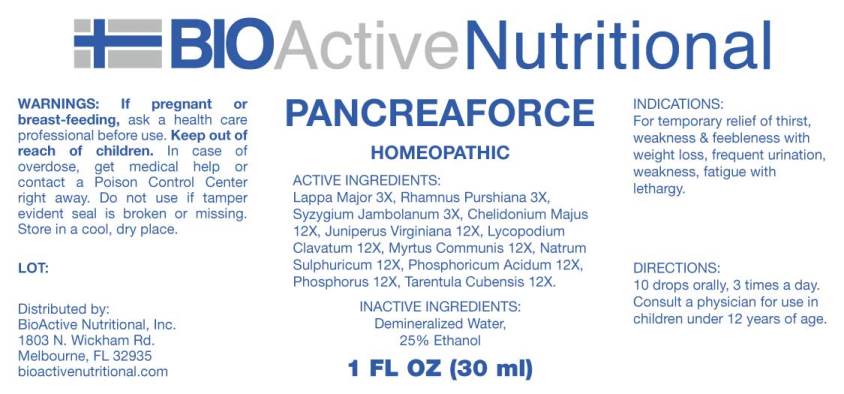 DRUG LABEL: Pancreaforce
NDC: 43857-0494 | Form: LIQUID
Manufacturer: BioActive Nutritional, Inc.
Category: homeopathic | Type: HUMAN OTC DRUG LABEL
Date: 20180831

ACTIVE INGREDIENTS: ARCTIUM LAPPA ROOT 3 [hp_X]/1 mL; FRANGULA PURSHIANA BARK 3 [hp_X]/1 mL; SYZYGIUM CUMINI SEED 3 [hp_X]/1 mL; CHELIDONIUM MAJUS 12 [hp_X]/1 mL; JUNIPERUS VIRGINIANA TWIG 12 [hp_X]/1 mL; LYCOPODIUM CLAVATUM SPORE 12 [hp_X]/1 mL; MYRTUS COMMUNIS TOP 12 [hp_X]/1 mL; SODIUM SULFATE 12 [hp_X]/1 mL; PHOSPHORIC ACID 12 [hp_X]/1 mL; PHOSPHORUS 12 [hp_X]/1 mL; CITHARACANTHUS SPINICRUS 12 [hp_X]/1 mL
INACTIVE INGREDIENTS: WATER; ALCOHOL

Drug Facts:

ACTIVE INGREDIENTS:

Lappa Major 3X, Rhamnus Purshiana 3X, Syzygium Jambolanum 3X, Chelidonium Majus 12X, Juniperus Virginiana 12X, Lycopodium Clavatum 12X, Myrtus Communis 12X, Natrum Sulphuricum 12X, Phosphoricum Acidum 12X, Phosphorus 12X, Tarentula Cubensis 12X.

INDICATIONS:

For temporary relief of thirst, weakness & feebleness with weight loss, frequent urination, weakness, fatigue with lethargy.

WARNINGS:

If pregnant or breast-feeding, ask a health care professional before use.

Keep out of reach of children. In case of overdose, get medical help or contact a Poison Control Center right away.

Do not use if tamper evident seal is broken or missing.

Store in cool, dry place.

Keep out of reach of children. In case of overdose, get medical help or contact a Poison Control Center right away.

DIRECTIONS:

10 drops orally, 3 times a day. Consult a physician for use in children under 12 years of age.

INDICATIONS:

For temporary relief of thirst, weakness & feebleness with weight loss, frequent urination, weakness, fatigue with lethargy.

INACTIVE INGREDIENTS:

Demineralized Water, 25% Ethanol.

QUESTIONS:

Distributed by:
BioActive Nutritional, Inc.
1803 N. Wickham Rd.
Melbourne, FL 32935
bioactivenutritional.com

PACKAGE DISPLAY LABEL:

BIOActive Nutritional

PANCREAFORCE

HOMEOPATHIC

1 FL OZ (30 ml)